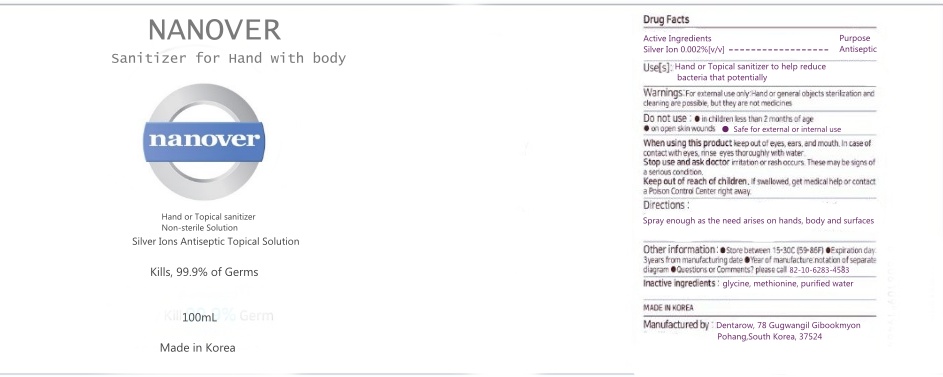 DRUG LABEL: NANOVER
NDC: 80577-301 | Form: SPRAY
Manufacturer: Korean Algae Association
Category: otc | Type: HUMAN OTC DRUG LABEL
Date: 20201010

ACTIVE INGREDIENTS: SILVER CATION 0.02 g/100 mL
INACTIVE INGREDIENTS: WATER 99.99 mL/100 mL; METHIONINE 0.01 mL/100 mL; GLYCINE 0.07 mL/100 mL

Active ingredien

SILVER CATION

USE

Hand or Topical sanitizer to help reduce bacteria that potentially.

WHEN USING

keep out of eyes, ears, and mouth. In case of contact with eyes, rinse eyes thoroughly with water.

Warnings

Innocuous

For external use only. Flammable. Keep away from heat or flame

Don't put it on your face Hand sterilization and cleaning are possible, but they are not medicines

Do not use

Safe for external or internal use.

in children less than 2 months of age

on open skin wounds

Stop use and ask doctor irritation or rash occurs. These may be signs of a serious condition.

If you experience any of the following problems, do not use this product and contact your dermatologist, etc

In case of abnormalities such as red spots, swelling,itching, irritation, etc. during use

PURPOSE

Antiseptic

Keep out of reach of children

Direction

Spray enough as the need arises on hands, body and surfaces.

Other information

Store between 15-30C (59-86F)

●Avoid freezing and excessive heat above 40C (104F)

●Year of manufacture:notation of separate diagram

●Expiration day:3years from manufacturing date

●Questions or Comments? please call 82-10-6283-4583

Inactive ingredient

Distilled water, Glycine, Methionine

label

80577-301-01